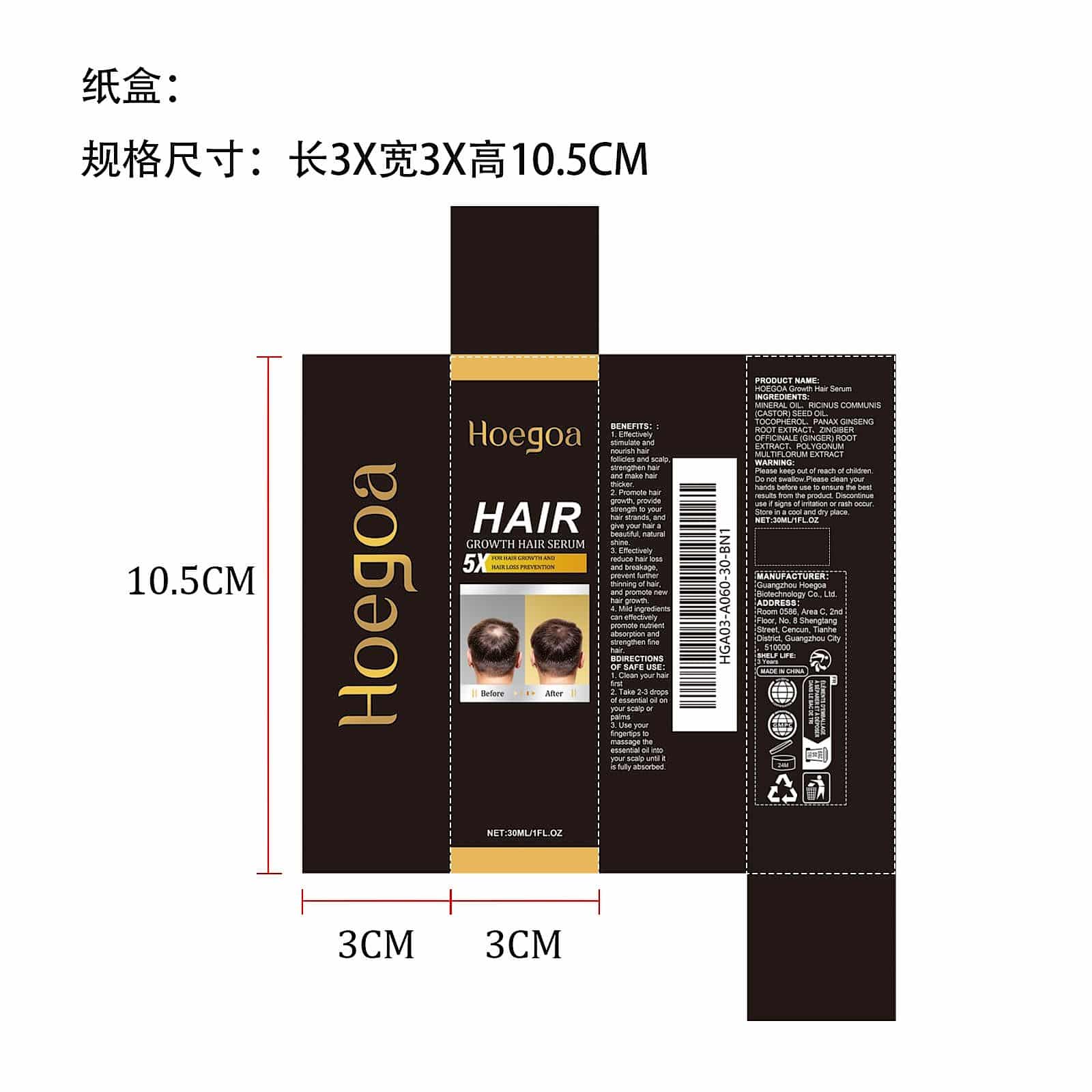 DRUG LABEL: HOEGOA Growth Hair Serum
NDC: 85064-021 | Form: LIQUID
Manufacturer: Shantou Oralhoe Biotechnology Co., Ltd.
Category: otc | Type: HUMAN OTC DRUG LABEL
Date: 20251129

ACTIVE INGREDIENTS: PANAX GINSENG ROOT OIL 0.006 mg/30 mg; POLYGONATUM MULTIFLORUM ROOT 0.006 mg/30 mg; RICINUS COMMUNIS (CASTOR) SEED OIL 9 mg/30 mg; ZINGIBER OFFICINALE (GINGER) ROOT OIL 0.006 mg/30 mg
INACTIVE INGREDIENTS: TOCOPHEROL 0.03 mg/30 mg; MINERAL OIL 20.952 mg/30 mg

ACTIVE INGREDIENT

MINERAL OIL、TOCOPHEROL

PURPOSE

1. Effectively stimulate and nourish hair follicles and scalp, strengthen hair and make hair thicker.

2. Promote hair growth, provide strength to your hair strands, and give your hair a beautiful, natural shine.

3. Effectively reduce hair loss and breakage, prevent further thinning of hair, and promote new hair growth.

4. Mild ingredients can effectively promote nutrient absorption and strengthen fine hair.

WHEN USING

1. Clean your hair first

2. Take 2-3 drops of essential oil on your scalp or palms

3. Use your fingertips to massage the essential oil into your scalp until it is fully absorbed.

WARNINGS

Please keep out of reach of children. Do not swallow.Please clean your hands before use to ensure the best results from the product. Discontinue use if signs of irritation or rash occur. Store in a cool and dry place.

DO NOT USE

Discontinue use if signs of irritation or rash occur.

STOP USE

Discontinue use if signs of irritation or rash occur.

KEEP OUT OF REACH OF CHILDREN

Please keep out of reach of children. Do not swallow.

STORAGE AND HANDLING

Store in a cool and dry place.

INACTIVE INGREDIENT

RICINUS COMMUNIS (CASTOR) SEED OIL、PANAX GINSENG ROOT EXTRACT、ZINGIBER OFFICINALE (GINGER) ROOT EXTRACT、POLYGONUM MULTIFLORUM EXTRACT

INDICATIONS AND USAGE

1. Clean your hair first

2. Take 2-3 drops of essential oil on your scalp or palms

3. Use your fingertips to massage the essential oil into your scalp until it is fully absorbed.

DOSAGE AND ADMINISTRATION

1. Clean your hair first

2. Take 2-3 drops of essential oil on your scalp or palms

3. Use your fingertips to massage the essential oil into your scalp until it is fully absorbed.